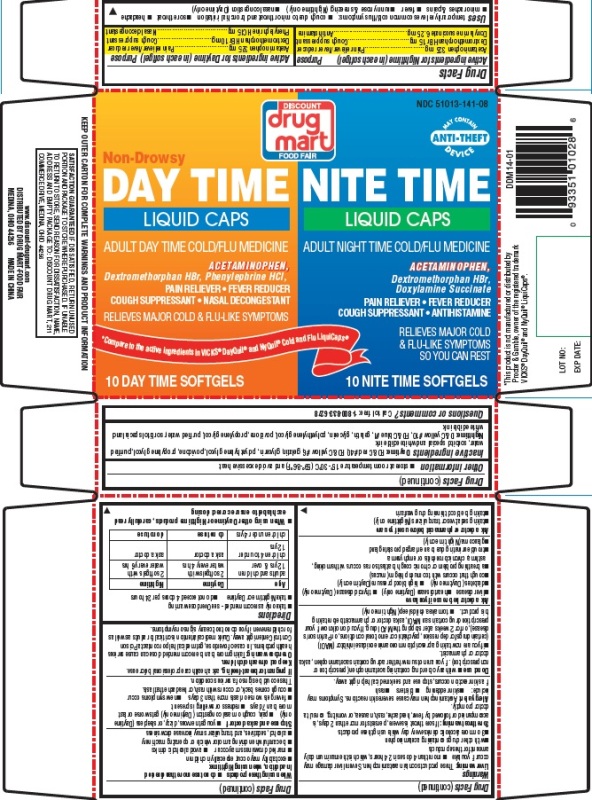 DRUG LABEL: DDM Day time and Nite time cold and flu
NDC: 51013-141 | Form: KIT | Route: ORAL
Manufacturer: PuraCap Pharmaceutical LLC
Category: otc | Type: HUMAN OTC DRUG LABEL
Date: 20191220

ACTIVE INGREDIENTS: ACETAMINOPHEN 325 mg/1 1; DEXTROMETHORPHAN HYDROBROMIDE 10 mg/1 1; PHENYLEPHRINE HYDROCHLORIDE 5 mg/1 1; ACETAMINOPHEN 325 mg/1 1; DEXTROMETHORPHAN HYDROBROMIDE 15 mg/1 1; DOXYLAMINE SUCCINATE 6.25 mg/1 1
INACTIVE INGREDIENTS: FD&C RED NO. 40; FD&C YELLOW NO. 6; GELATIN; GLYCERIN; POLYETHYLENE GLYCOL, UNSPECIFIED; POVIDONE; PROPYLENE GLYCOL; WATER; SORBITOL; D&C YELLOW NO. 10; FD&C BLUE NO. 1; GELATIN; GLYCERIN; POLYETHYLENE GLYCOL, UNSPECIFIED; POVIDONE; PROPYLENE GLYCOL; WATER; SORBITOL

DAY TIME and NITE TIME COLD/FLU LIQUID CAPS

Active ingredients (in each softgel)

Active ingredients for Nighttime (in each Softgel)

Acetaminophen 325 mg

Dextromethorphan HBr 15 mg

Doxylamine succinate 6.25 mg

Active ingredients for Daytime (in each Softgel)

Acetaminophen 325 mg

Dextromethorphan HBr 10 mg

Phenylephrine HCl 5 mg

Purposes

DDM NITE TIME COLD/FLU LIQUID CAPS

Pain reliever/fever reducer

Cough suppressant

Antihistamine

DDM DAY TIME COLD/FLU LIQUID CAPS

Pain reliever/fever reducer

Cough suppressant

Nasal decongestant

Uses

temporarily relieves common cold/flu symptoms:

- cough due to minor throat and bronchial irritation
- sore throat
- headache
- minor aches & pains
- fever
- runny nose & sneezing (Nighttime only)
- nasal congestion (Daytime only)

WARNINGS

Liver warning

These products contain acetaminophen. Severe liver damage may occur if you take

- more than 4 doses in 24 hrs, which is the maximum daily amount for these products
- with other drugs containing acetaminophen
- 3 or more alcoholic drinks every day while using these products

Sore throat warning

If sore throat is severe, persists for more than 2 days, is accompanied or followed by fever, headache, rash, nausea, or vomiting, consult a doctor promptly.

Allergy alert: Acetaminophen may cause severe skin reactions. Symptoms may include:

- skin reddening
- blisters
- rash

If a skin reaction occurs, stop use and seek medical help right away.

Do not use

- with any other drug containing acetaminophen (prescription or nonprescription). If you are not sure whether a drug contains acetaminophen, ask a doctor or pharmacist.
- if you are now taking a prescription monoamine oxidase inhibitor (MAOI) (certain drugs for depression, psychiatric or emotional conditions, or Parkinson's disease), or for 2 weeks after stopping the MAOI drug. If you do not know if your prescription drug contains an MAOI, ask a doctor or pharmacist before taking this product.
- to make a child sleep (Nighttime only)

Ask a doctor before use if you have

- liver disease
- heart disease (Daytime only)
- thyroid disease (Daytime only)
- diabetes (Daytime only)
- high blood pressure (Daytime only)
- cough that occurs with too much phlegm (mucus)
- a breathing problem or chronic cough that lasts or as occurs with smoking, asthma, chronic bronchitis or emphysema
- trouble urinating due to an enlarged prostate gland
- glaucoma (Nighttime only)

Ask a doctor or pharmacist before use if you are

- taking sedatives or tranquilizers (Nighttime only)
- taking the blood thinning drug warfarin

When using these products

- do not use more than directed

In addition, when using Nighttime:

- excitability may occur, especially in children
- marked drowsiness may occur
- avoid alcoholic drinks
- be careful when driving a motor vehicle or operating machinery
- alcohol, sedatives, and tranquilizers may increase drowsiness

Stop use and ask a doctor if

- you get nervous, dizzy, or sleepless (Daytime only)
- pain, cough or nasal congestion (Daytime only) gets worse or last more than 7 days
- redness or swelling is present
- fever gets worse or lasts more than 3 days
- new symptoms occur
- cough comes back, or occurs with rash, or headache that lasts.

These could be signs of a serious condition.

PREGNANCY OR BREAST FEEDING

If pregnant or breast-feeding, ask a health professional before use.

Keep out of reach of children.

Overdose warning:

Taking more than the recommended dose can cause serious health problems. In case of overdose, get medical help or contact a Poison Control Center right away. Quick medical attention is critical for adults as well as for children even if you do not notice any signs or symptoms.

Directions

- take only as directed - see Overdose warning
- Take Nighttime or Daytime
- do not exceed 4 doses per 24 hrs

Age | Daytime | Nighttime
adults and children 12 yrs & over | 2 softgels with water every 4 hrs | 2 softgels with water every 6 hrs
children 4 to under 12 yrs | ask a doctor | ask a doctor
children under 4 yrs | do not use | do not use

- When using other Daytime or Nighttime products, carefully read each label to ensure correct dosing

Other information

- store at room temperature 15°-30°C (59°-86°F) and avoid excessive heat

Inactive ingredients

Daytime: FD&C red #40, FD&C yellow #6, gelatin, glycerin, polyethylene glycol, povidone, propylene glycol, purified water, sorbitol special and white edible ink

Nighttime: D&C yellow # 10, FD&C blue #1, gelatin, glycerin, polyethylene glycol, povidone, propylene glycol, purified water, sorbitol special and white edible ink

Questions or comments?

Call toll free: 1-800-833-6278

Principle Display Panel

DDM DAT TIME and NITE TIME COLD/FLU LIQUID CAPS

NDC 51013-141-08

*Compare to the active ingredients in VICKS® DayQuil® and NyQuil® Cold and Flu LiquiCaps®